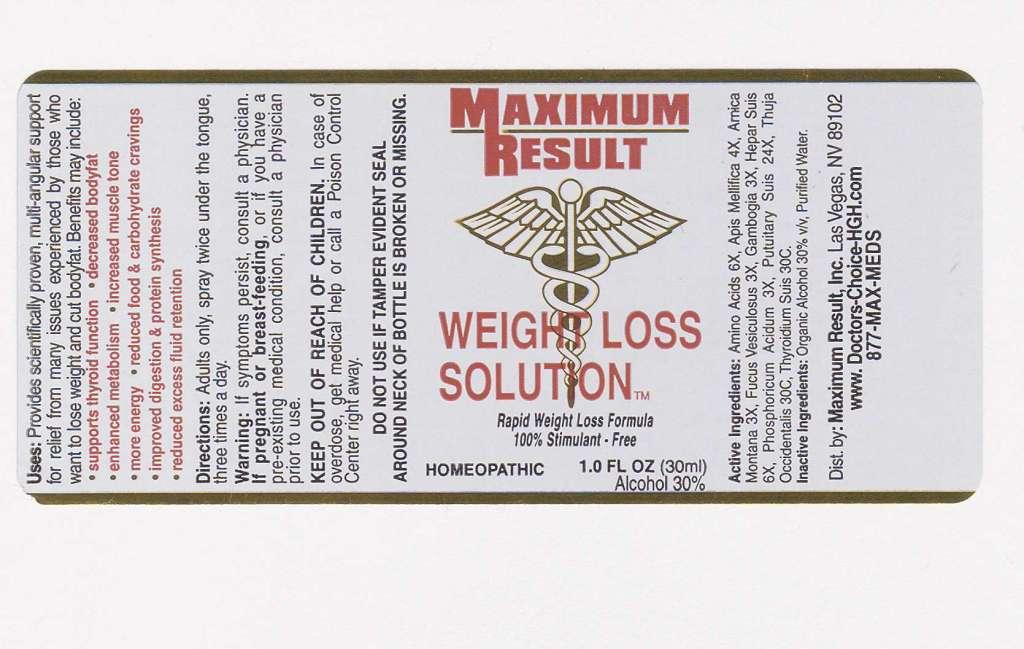 DRUG LABEL: Weight Loss Solution
NDC: 50845-0037 | Form: SPRAY
Manufacturer: Liddell Laboratories
Category: homeopathic | Type: HUMAN OTC DRUG LABEL
Date: 20100811

ACTIVE INGREDIENTS: AMINO ACIDS 6 [hp_X]/1 mL; APIS MELLIFERA 4 [hp_X]/1 mL; ARNICA MONTANA 3 [hp_X]/1 mL; FUCUS VESICULOSUS 3 [hp_X]/1 mL; GAMBOGE 3 [hp_X]/1 mL; PORK LIVER 6 [hp_X]/1 mL; PHOSPHORIC ACID 3 [hp_X]/1 mL; SUS SCROFA PITUITARY GLAND 24 [hp_X]/1 mL; THUJA OCCIDENTALIS LEAFY TWIG 30 [hp_C]/1 mL; SUS SCROFA THYROID 30 [hp_C]/1 mL
INACTIVE INGREDIENTS: WATER; ALCOHOL

Weight Loss Solution

ACTIVE INGREDIENT

ACTIVE INGREDIENTS: Amino acids 6X, Apis mellifica 4X, Arnica montana 3X, Fucus vesiculosus 3X, Gambogia 3X, Hepar suis 6X, Phosphoricum acidum 3X, Pituitary suis 24X, Thuja occidentalis 30C, Thyroidinum suis 30C.

PURPOSE

USES: Provides scientifically proven, multi-angular support for relief from many issues experienced by those who want to lose weight and cut bodyfat. Benefits may include: *support thyroid function *decreased bodyfat *enhanced metabolism *increased muscle tone *more energy *reduced food and carbohydrate cravings *improved digestion and protein synthesis *reduced excess fluid retention.

WARNINGS

WARNING: If symptoms persist, consult a physician. If pregnant or breast-feeding, or if you have a pre-existing medical condition, consult a physician prior to use.

Keep out of reach of children. In case of overdose, get medical help or call a Poison Control Center right away.

DO NOT USE IF TAMPER EVIDENT SEAL AROUND NECK OF BOTTLE IS BROKEN OR MISSING.

DOSAGE AND ADMINISTRATION

DIRECTIONS: Adults only, spray twice under the tongue, three times a day.

INACTIVE INGREDIENT

INACTIVE INGREDIENTS: Organic alcohol 30% v/v, Purified water.

QUESTIONS

Dist. by:

Maximum Result, Inc.

Las Vegas, NV 89102

www.Doctors-Choice-HGH.com

877-MAX-MEDS

PACKAGE LABEL

MAXIMUM RESULT

WEIGHT LOSS SOLUTION

Rapid Weight Loss Formula

100% Stimulant-Free

HOMEOPATHIC

1.0 FL OZ (30 ml)